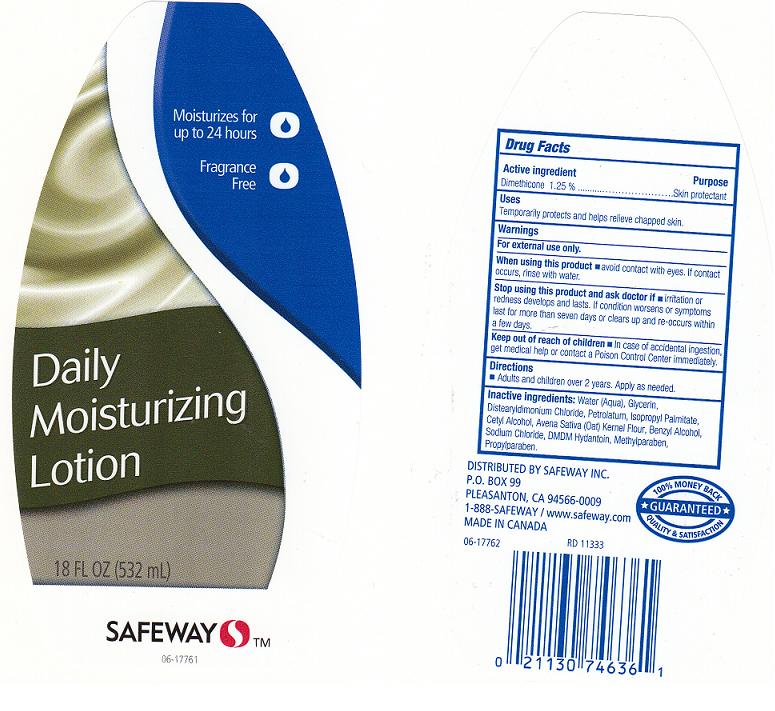 DRUG LABEL: SAFEWAY
NDC: 21130-320 | Form: LOTION
Manufacturer: SAFEWAY INC.
Category: otc | Type: HUMAN OTC DRUG LABEL
Date: 20111215

ACTIVE INGREDIENTS: DIMETHICONE 1.25 mL/100 mL
INACTIVE INGREDIENTS: WATER; GLYCERIN; DISTEARYLDIMONIUM CHLORIDE; PETROLATUM; ISOPROPYL PALMITATE; CETYL ALCOHOL; OATMEAL; BENZYL ALCOHOL; SODIUM CHLORIDE; DMDM HYDANTOIN; METHYLPARABEN; PROPYLPARABEN

DRUG FACTS

ACTIVE INGREDIENT

DIMETHICONE 1.25%

PURPOSE

SKIN PROTECTANT

USES

TEMPORARILY PROTECTS AND HELPS RELIEVE CHAPPED SKIN.

WARNINGS

FOR EXTERNAL USE ONLY.

WHEN USING THIS PRODUCT

AVOID CONTACT WITH EYES. IF CONTACT OCCURS, RINSE WITH WATER.

STOP USING THIS PRODUCT AND ASK DOCTOR IF

IRRITATION OR REDNESS DEVELOPS AND LASTS. IF CONDITION WORSENS OR SYMPTOMS LAST FOR MORE THAN SEVEN DAYS OR CLEARS UP AND RE-OCCURS WITHIN A FEW DAYS.

KEEP OUT OF REACH OF CHILDREN

IN CASE OF ACCIDENTAL INGESTION, GET MEDICAL HELP OR CONTACT A POISON CONTROL CENTER IMMEDIATELY.

DIRECTIONS

ADULTS AND CHILDREN OVER 2 YEARS. APPLY AS NEEDED.

INACTIVE INGREDIENTS:

WATER (AQUA), GLYCERIN, DISTEARYLDIMONIUM CHLORIDE, PETROLATUM, ISOPROPYL PALMITATE, CETYL ALCOHOL, AVENA SATIVA (OAT) KERNEL FLOUR, BENZYL ALCOHOL, SODIUM CHLORIDE, DMDM HYDANTOIN, METHYLPARABEN, PROPYLPARABEN.